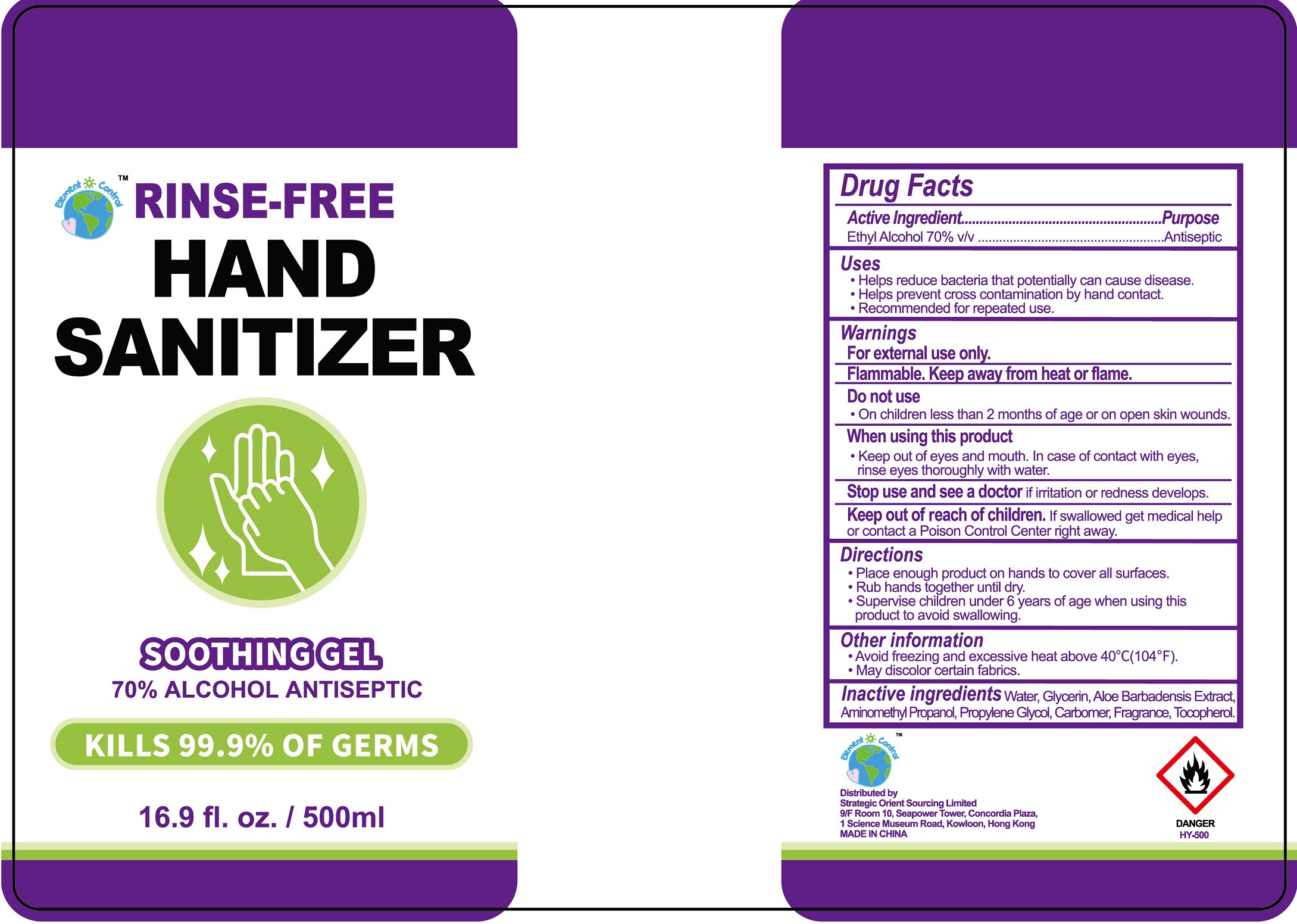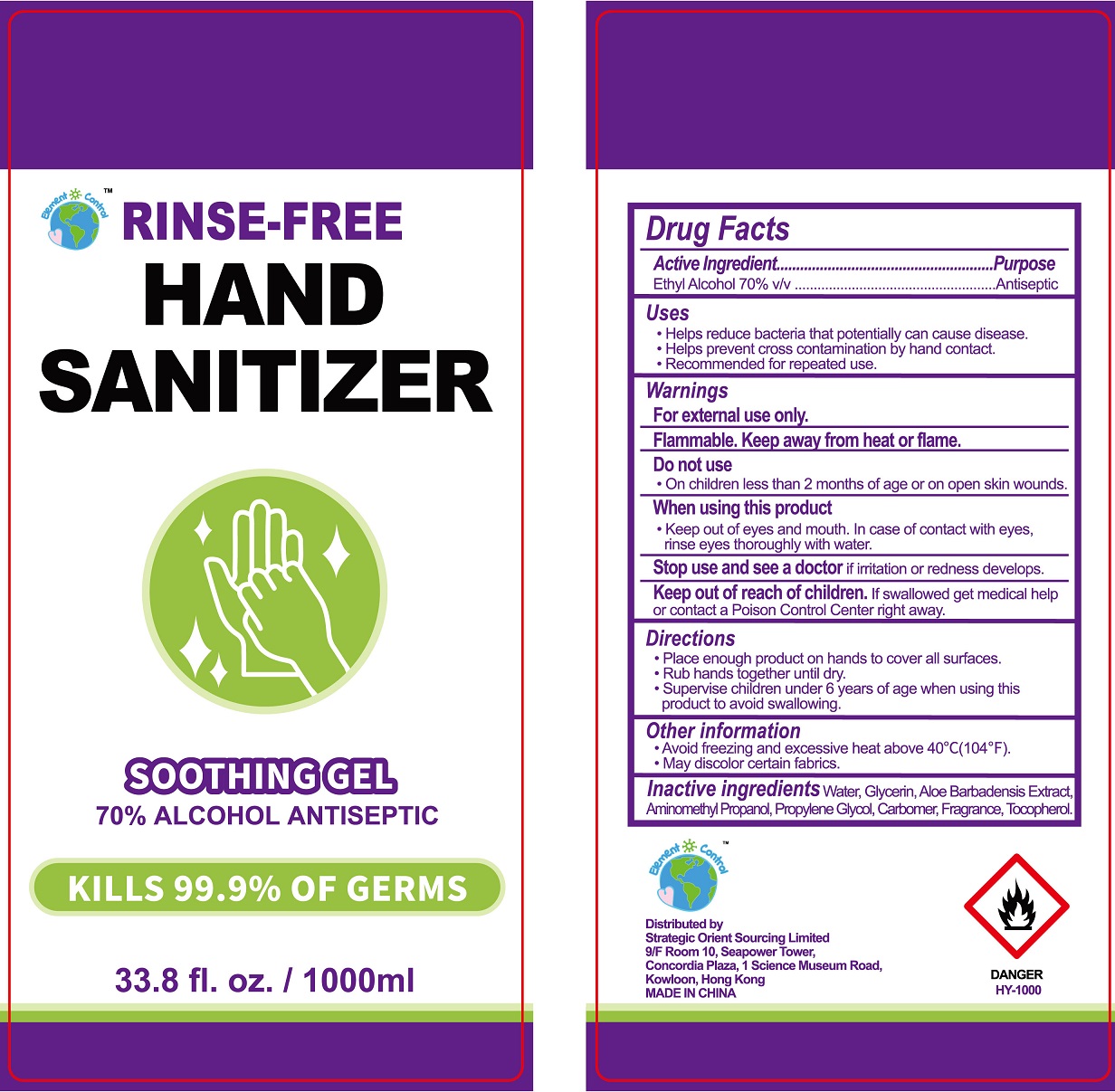 DRUG LABEL: Hand sanitizer
NDC: 79995-002 | Form: GEL
Manufacturer: STRATEGIC ORIENT SOURCING LIMITED
Category: otc | Type: HUMAN OTC DRUG LABEL
Date: 20200805

ACTIVE INGREDIENTS: ALCOHOL 0.7 mL/1 mL
INACTIVE INGREDIENTS: WATER; GLYCERIN; ALOE VERA LEAF; AMINOMETHYLPROPANOL; CARBOMER HOMOPOLYMER, UNSPECIFIED TYPE; TOCOPHEROL

Hand sanitizer

Active Ingredient

Ethyl Alcohol 70% v/v

Purpose

Antiseptic

Uses

- Helps reduce bacteria that potentially can cause disease.
- Helps prevent cross contamination by hand contact.
- Recommended for repeated use.

Warnings

For external use only.

Flammable. Keep away from heat or flame.

Do not use

- On children less than 2 months of age or on open skin wounds.

When using this product

- Keep out of eyes and mouth. In case of contact with eyes, rinse eyes thoroughly with water.

Stop use and see a doctor

if irritation or redness develops.

Keep out of reach of children.

If swallowed get medical help or contact a Poison Control Center right away.

Directions

- Place enough product on hands to cover all surfaces.
- Rub hands together until dry.
- Supervise children under 6 years of age when using this product to avoid swallowing.

Other information

- Avoid freezing and excessive heat above 40°C(104°F).
- May discolor certain fabrics.

Inactive ingredients

Water, Glycerin, Aloe Barbadensis Extract, Aminomethyl Propanol, Carbomer, Fragrance, Tocopherol.